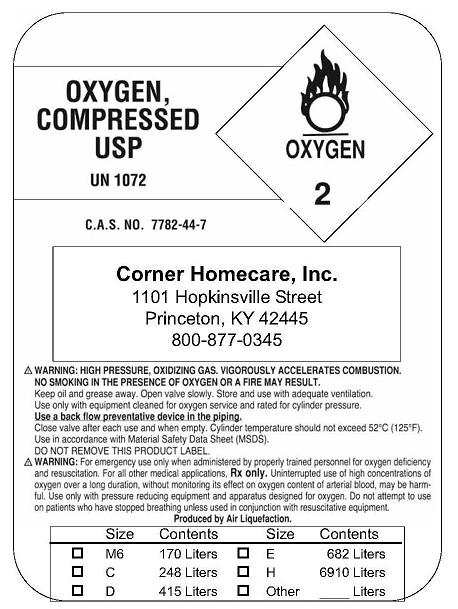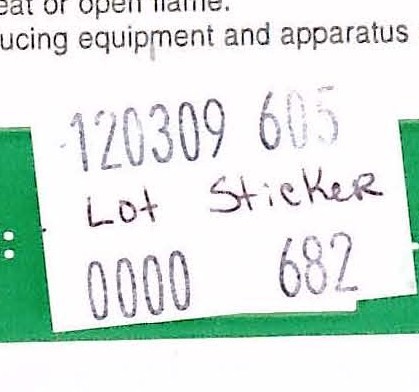 DRUG LABEL: Oxygen
NDC: 64588-0001 | Form: GAS
Manufacturer: Corner Homecare
Category: prescription | Type: HUMAN PRESCRIPTION DRUG LABEL
Date: 20091223

ACTIVE INGREDIENTS: Oxygen 99 L/100 L

Oxygen